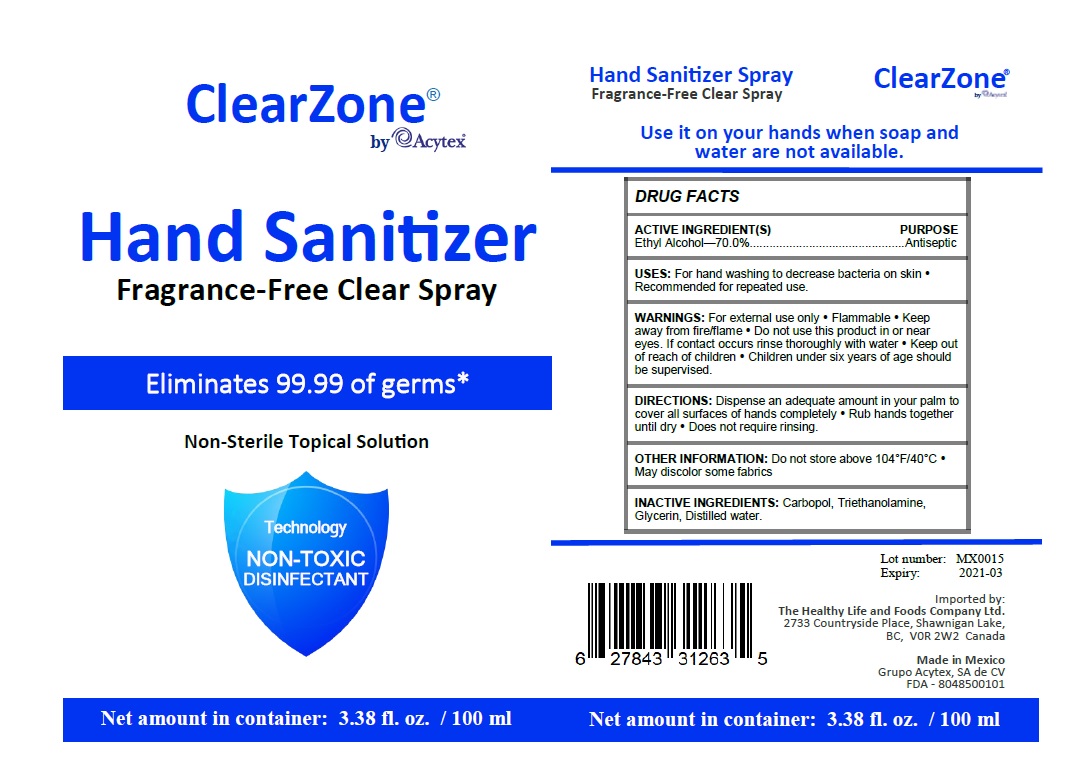 DRUG LABEL: ClearZone Hand Sanitizer
NDC: 80485-001 | Form: SPRAY
Manufacturer: Grupo Acytex, S.A. de C.V.
Category: otc | Type: HUMAN OTC DRUG LABEL
Date: 20200928

ACTIVE INGREDIENTS: ALCOHOL 70 mL/100 mL
INACTIVE INGREDIENTS: CARBOMER HOMOPOLYMER, UNSPECIFIED TYPE; TROLAMINE; GLYCERIN; WATER

ClearZone® Hand Sanitizer

ACTIVE INGREDIENT(S)

Ethyl Alcohol—70.0%

PURPOSE

Antiseptic

INDICATIONS AND USAGE

USES: For hand washing to decrease bacteria on skin • Recommended for repeated use.

WARNINGS

WARNINGS: For external use only • Flammable • Keep away from fire/flame • Do not use this product in or near eyes. If contact occurs rinse thoroughly with water

• Keep out of reach of children • Children under six years of age should be supervised.

DOSAGE AND ADMINISTRATION

DIRECTIONS: Dispense an adequate amount in your palm to cover all surfaces of hands completely • Rub hands together until dry • Does not require rinsing.

OTHER INFORMATION: Do not store above 104°F/40°C • May discolor some fabrics

INACTIVE INGREDIENT

INACTIVE INGREDIENTS: Carbopol, Triethanolamine, Glycerin, Distilled water.

Fragrance-Free Clear Spray

Eliminates 99.99 of germs*

Non-Sterile Topical Solution

Technology
NON-TOXIC
DISINFECTANT

Use it on your hands when soap and water are not available.

Imported by:
The Healthy Life and Foods Company Ltd.2733 Countryside Place, Shawnigan Lake,
BC, V0R 2W2 Canada

Made in Mexico

Grupo Acytex, SA de CV